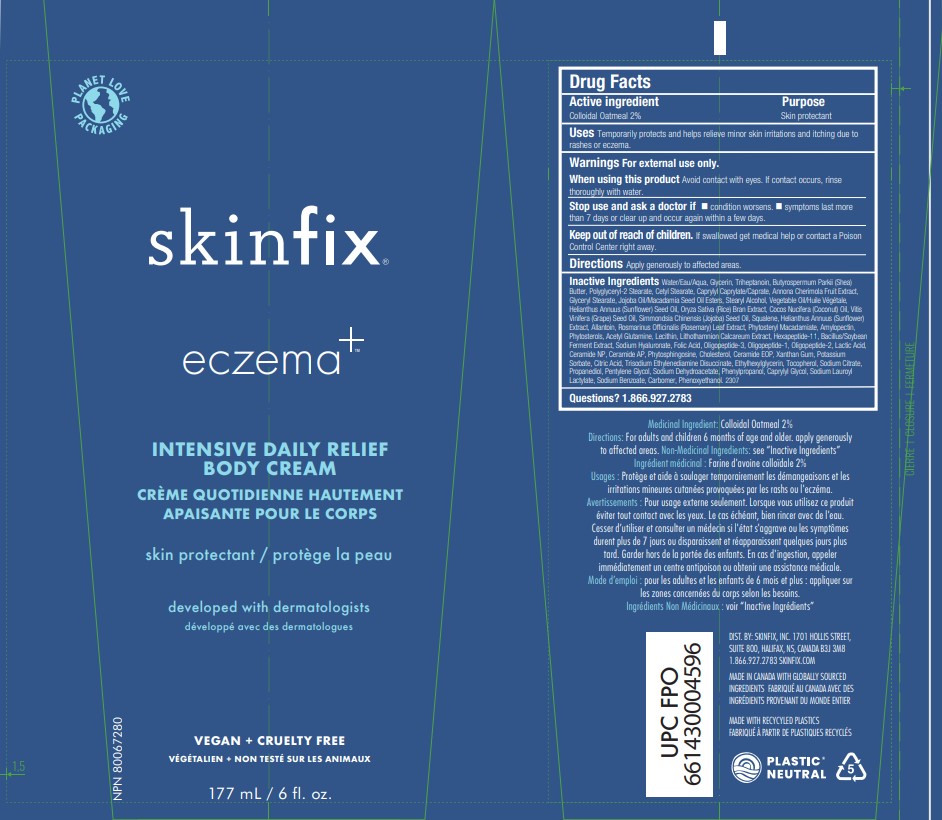 DRUG LABEL: ECZEMA INTENSIVE DAILY RELIEF BODY
NDC: 61328-210 | Form: CREAM
Manufacturer: Skinfix, Inc.
Category: otc | Type: HUMAN OTC DRUG LABEL
Date: 20260112

ACTIVE INGREDIENTS: OATMEAL 2 g/100 g
INACTIVE INGREDIENTS: ETHYLHEXYLGLYCERIN; TRISODIUM ETHYLENEDIAMINE DISUCCINATE; AMYLOPECTIN, UNSPECIFIED SOURCE; CERAMIDE NP; CETYL STEARATE; CHERIMOYA; SODIUM DEHYDROACETATE; PHYMATOLITHON CALCAREUM; CERAMIDE AP; SODIUM BENZOATE; WATER; GLYCERIN; SQUALENE; SUNFLOWER SEED; SHEA BUTTER; MACADAMIA SEED OIL GLYCERETH-8 ESTERS; XANTHAN GUM; ROSEMARY; PHENYLPROPANOL; CARBOMER HOMOPOLYMER, UNSPECIFIED TYPE; PROPANEDIOL; LACTIC ACID; CHOLESTEROL; ACEGLUTAMIDE; SODIUM LAUROYL LACTYLATE; CAPRYLYL CAPRYLATE/CAPRATE; RICE BRAN; COCONUT OIL; ALLANTOIN; TOCOPHEROL; SODIUM CITRATE; PHYTOSPHINGOSINE; POLYGLYCERYL-2 STEARATE; CITRIC ACID MONOHYDRATE; LECITHIN, SOYBEAN; PENTYLENE GLYCOL; STEARYL ALCOHOL; CORN OIL; PHENOXYETHANOL; POTASSIUM SORBATE; JOJOBA OIL; PHYTOSTERYL MACADAMIATE; SOY STEROL; HYALURONATE SODIUM; FOLIC ACID; CAPRYLYL GLYCOL; SUNFLOWER OIL; GRAPE SEED OIL; HEXAPEPTIDE-11; CERAMIDE 1; TRIHEPTANOIN; GLYCERYL MONOSTEARATE

ECZEMA+ INTENSIVE DAILY RELIEF BODY CREAM

ACTIVE INGREDIENT

Colloidal Oatmeal 2%

INDICATIONS AND USAGE

Temporarily protects and helps relieve minor skin irritations and itching due to rashes or eczema.

RECENT MAJOR CHANGES

Temporarily protects and helps relieve minor skin irritations and itching due to rashes or eczema.

PURPOSE

Skin protectant

WARNINGS

For external use only.

When using this product avoid contact with eyes. if contact occurs, rinse thoroughly with water.

KEEP OUT OF REACH OF CHILDREN

If swallowed get medical help or contact a poison control center right away.

STOP USE

condition worsens
symptoms last more than 7 days or clear up and occur again within a few days

DOSAGE AND ADMINISTRATION

Apply generously to affected areas.

INACTIVE INGREDIENT

Water/Eau/Aqua, Glycerin, Triheptanoin, Butyrospermum Parkii (Shea) Butter, Polyglyceryl-2 Stearate, Cetyl Stearate, Caprylyl Caprylate/Caprate, Annona Cherimola Fruit Extract, Glyceryl Stearate, Jojoba Oil/Macadamia Seed Oil Esters, Stearyl Alcohol, Vegetable Oil/Huile Végétale, Helianthus Annuus (Sunflower) Seed Oil, Oryza Sativa (Rice) Bran Extract, Cocos Nucifera (Coconut) Oil, Vitis Vinifera (Grape) Seed Oil, Simmondsia Chinensis (Jojoba) Seed Oil, Squalene, Helianthus Annuus (Sunflower) Extract, Allantoin, Rosmarinus Officinalis (Rosemary) Leaf Extract, Phytosteryl Macadamiate, Amylopectin, Phytosterols, Acetyl Glutamine, Lecithin, Lithothamnion Calcareum Extract, Hexapeptide-11, Bacillus/Soybean Ferment Extract, Sodium Hyaluronate, Folic Acid, Oligopeptide-3, Oligopeptide-1, Oligopeptide-2, Lactic Acid, Ceramide NP, Ceramide AP, Phytosphingosine, Cholesterol, Ceramide EOP, Xanthan Gum, Potassium Sorbate, Citric Acid, Trisodium Ethylenediamine Disuccinate, Ethylhexylglycerin, Tocopherol, Sodium Citrate, Propanediol, Pentylene Glycol, Sodium Dehydroacetate, Phenylpropanol, Caprylyl Glycol, Sodium Lauroyl Lactylate, Sodium Benzoate, Carbomer, Phenoxyethanol.

QUESTIONS

1.866.927.2783

DOSAGE AND ADMINISTRATION

Apply generously to affected areas.